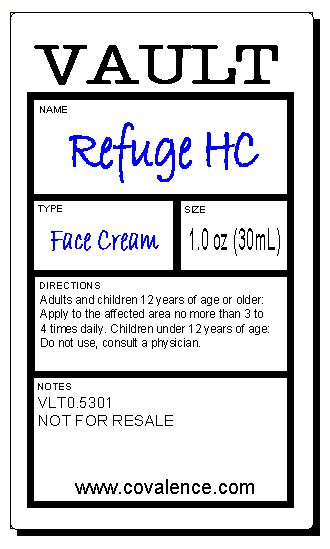 DRUG LABEL: Refuge HC
NDC: 66915-531 | Form: CREAM
Manufacturer: CoValence Inc.
Category: otc | Type: HUMAN OTC DRUG LABEL
Date: 20110818

ACTIVE INGREDIENTS: HYDROCORTISONE .01 mg/1 g
INACTIVE INGREDIENTS: WATER; GLYCERIN; MEDIUM-CHAIN TRIGLYCERIDES; CETEARYL OLIVATE; HEDYCHIUM CORONARIUM ROOT; LEVOMENOL; ROSA CANINA FRUIT OIL; SQUALANE; TOCOPHEROL; ALOE VERA LEAF; LONICERA CAPRIFOLIUM FLOWER; LONICERA JAPONICA FLOWER; SOYBEAN OIL; SORBITAN OLIVATE; XANTHAN GUM; PHYTIC ACID; CARBOMER 934; POTASSIUM SORBATE; SODIUM HYDROXIDE; GLUCONOLACTONE; SODIUM BENZOATE; CAPRYLYL GLYCOL; PHENYLETHYL ALCOHOL; TRISODIUM ETHYLENEDIAMINE DISUCCINATE

Drug Facts

Active Ingredient(s): Hydrocortisone 1%

Purpose: For itchy skin.

Keep out of reach of children. If swallowed, get medical help or contact a Poison Control Center right away. Children under 12 years of age: do not use, consult a physician.

INDICATIONS AND USAGE

Use: For temporary relief of itching and discomfort associated with minor skin irritations, inflammation and rashes.

WARNINGS

Warnings: For external use only. Avoid contact with eyes.

DOSAGE AND ADMINISTRATION

Directions: Adults and children 12 years of age or older: Apply to the affected area no more than 3 to 4 times daily.

INACTIVE INGREDIENT

Inactive Ingredients: Aqua (Water), Glycerin, Caprylic/Capric Triglyceride, Cetearyl Olivate, Hedychium Coronarium (White Giner) Root Extract, Bisabolol (L-alpha), Rosa Canina (Rose Hip) Fruit Oil, Squalane, Tocopherol (D-alpha), Aloe Barbadensis Leaf Juice Powder, Lonicera Caprifolium (Honeysuckle) Flower Extract, Lonicera Japonica (Honeysuckle) Flower Extract, Glycine Soja (Soybean) Oil, Sorbitan Olivate, Xanthan Gum, Phytic Acid, Carbomer, Potassium Sorbate, Sodium Hydroxide, Calcium Gluconate, Gluconolactone, Sodium Benzoate, Caprylyl Glycol, Phenethyl Alcohol, Trisodium Ethylenediamine Disuccinate

PACKAGE LABEL

Prinicpal Display Panel